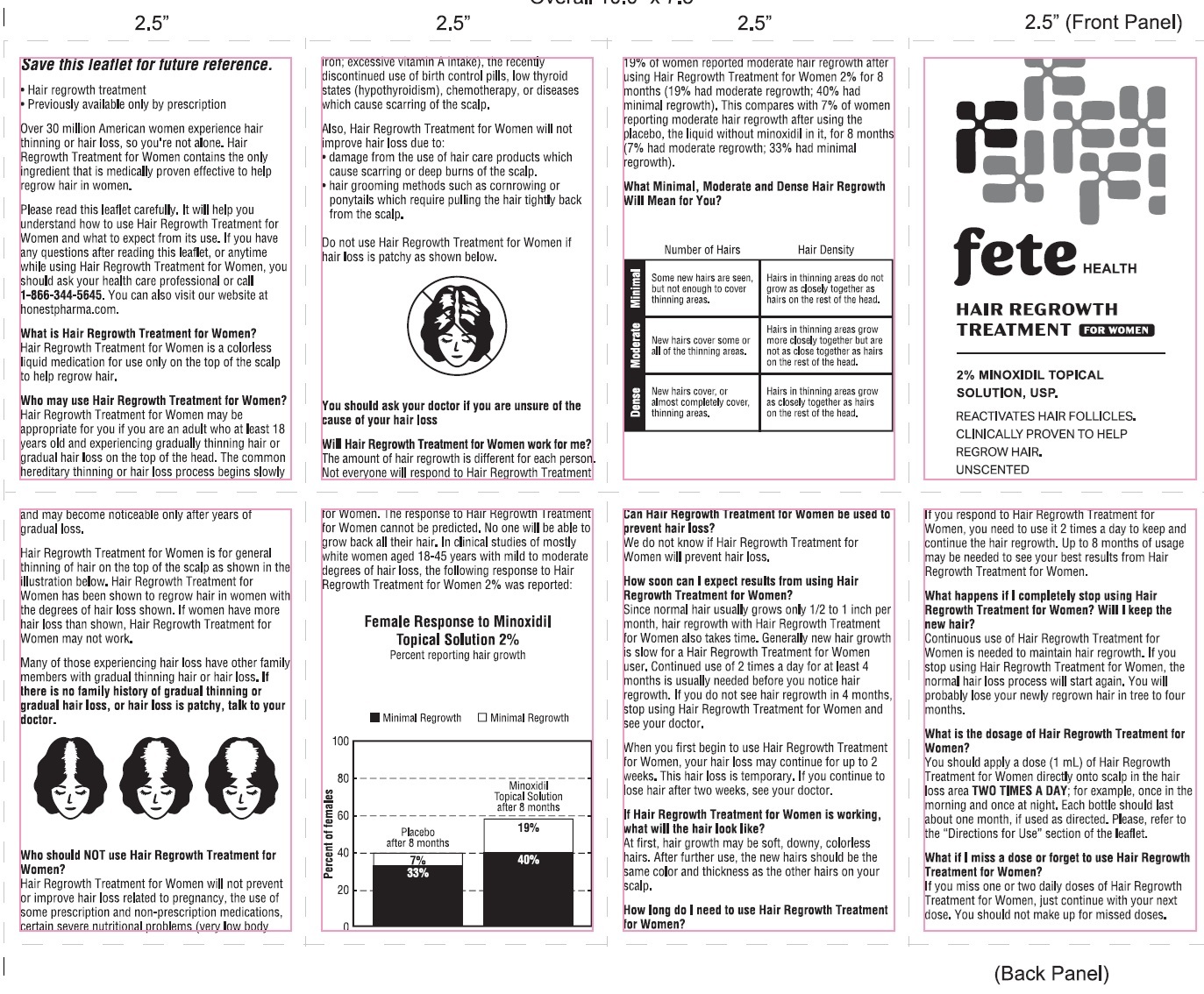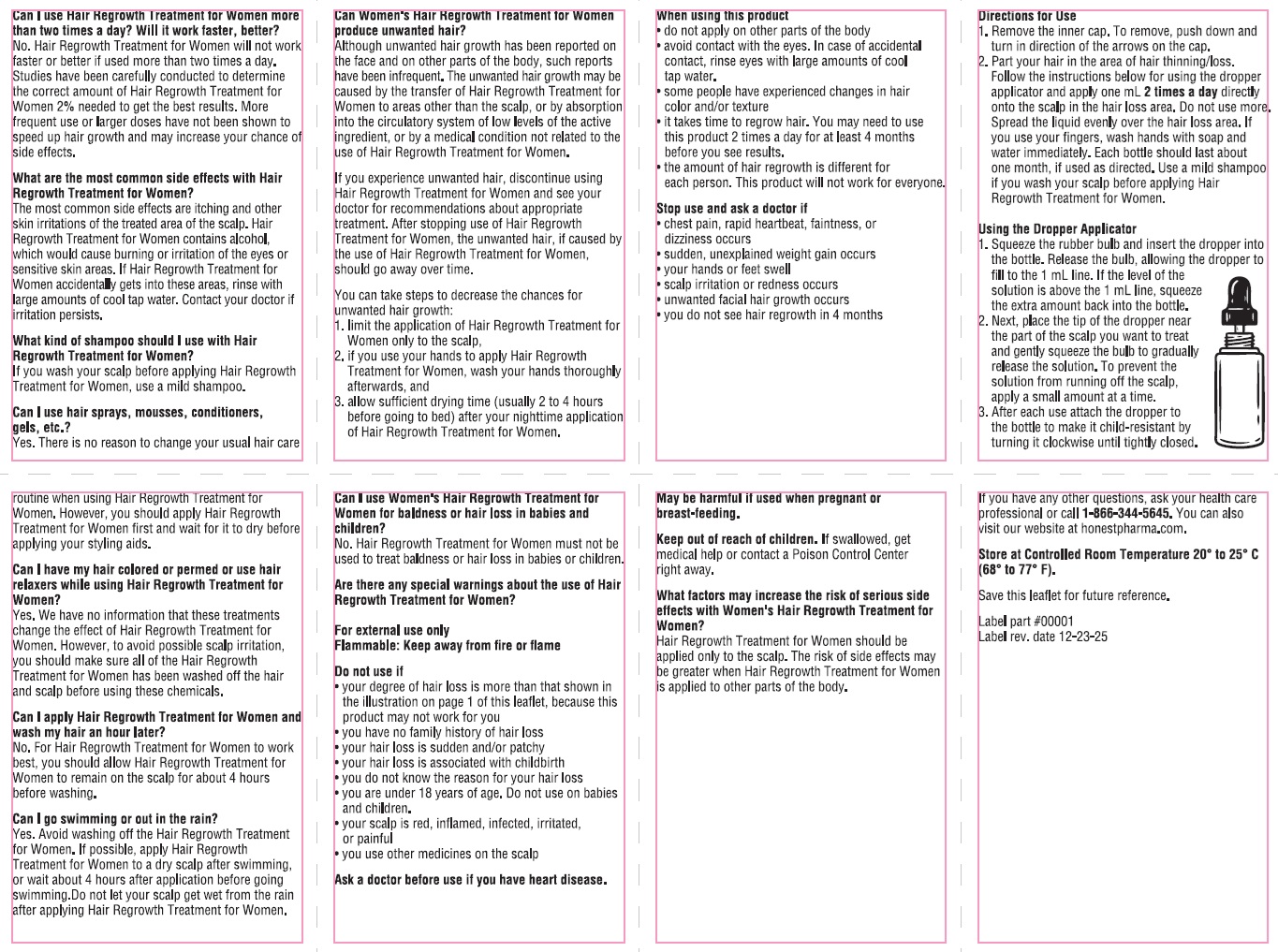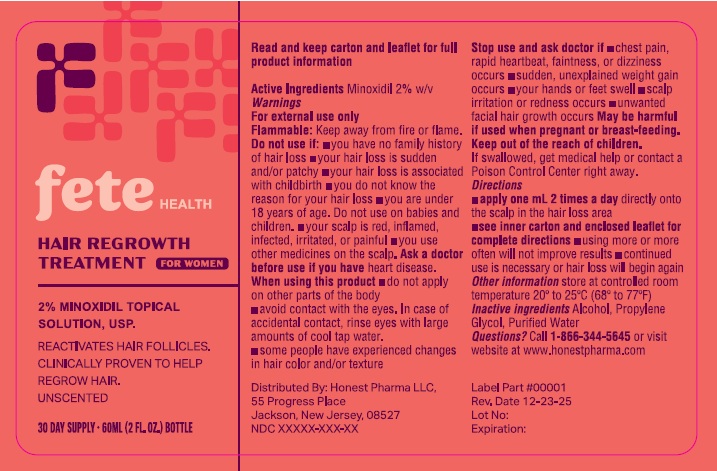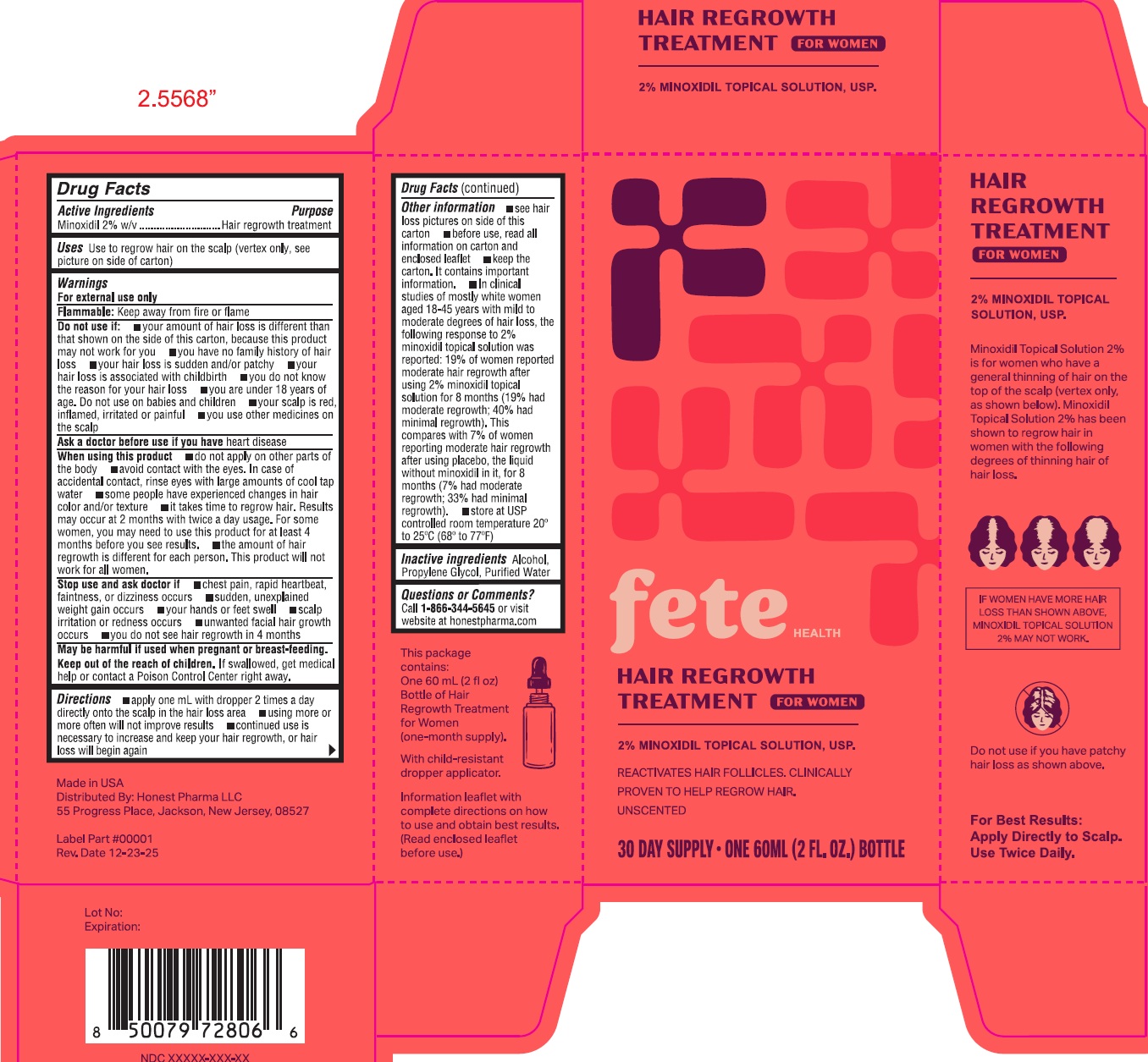 DRUG LABEL: Fete Health Hair Regrowth Treatment for Women
NDC: 87412-981 | Form: SOLUTION
Manufacturer: Honest Pharma LLC
Category: otc | Type: HUMAN OTC DRUG LABEL
Date: 20260211

ACTIVE INGREDIENTS: MINOXIDIL 20 mg/1 mL
INACTIVE INGREDIENTS: ALCOHOL; PROPYLENE GLYCOL; WATER

Fete Health Hair Regrowth Treatment for Women

Active ingredients

Minoxidil 2%

Purpose

Hair regrowth treatment

Uses

Use to regrow hair on the scalp (vertex only, see picture on side of carton)

Warnings

For external use only

Flammbel: keep away from fire or flame

Do not use if:

- your amount of hair loss is different than that shown on the side of this carton, because this product may not work for you
- you have no family history of hair loss
- your hair loss is sudden and/or patchy
- your hair loss is associated with childbirth
- you do not know the reason for your hair loss
- you are under 18 years of age. Do not use on babies and children
- your scalp is red, inflamed, irritated or painful
- you use other medicines on the scalp

Ask a doctor before use if you have

heart disease

When using this product

- do not apply on other parts of the body
- avoid contact with the eyes. In case of accidental contact, rinse eyes with large amounts of cool tap water
- some people have experienced changes in hair color and/or texture
- it takes time to regrow hair. Results may occur at 2 months with twice a day usage. For some women, you may need to use this product for at least 4 months before you see results.
- the amount of hair regrowth is different for each person. This product will not work for all women.

Stop use and ask doctor if

- chest pain, rapid heartbeat, faintness, or dizziness occurs
- sudden, unexplained weight gain occurs
- your hands or feet swell
- scalp irritation or redness occurs
- unwanted facial hair growth occurs
- you do not see hair regrowth in 4 months

Keep out of the reach of children.

If swallowed, get medical help or contact a Poison Control Center right away.

Directions

- apply one mL with dropper 2 times a day directly onto the scalp in the hair loss area
- using more or more often will not improve results
- continued use is necessary to increase and keep your hair regrowth, or hair loss will begin again

Other information

- see hair loss pictures on side of this carton
- before use, read all information on carton and enclosed leaflet
- keep the carton. It contains important information.
- In clinical studies of mostly white women aged 18-45 years with mild to moderate degrees of hair loss, the following response to 2% minoxidil topical solution was reported: 19% of women reported moderate hair regrowth after using 2% minoxidil topical solution for 8 months (19% had moderate regrowth; 40% had minimal regrowth). This compares with 7% of women reporting moderate hair regrowth after using placebo, the liquid without minoxidil in it, for 8 months (7% had moderate regrowth; 33% had minimal regrowth).
- store at USP controlled room temperature 200 to 250C (680 to 770F)

Inactive ingredients

Alcohol, Propylene Glycol, Purified Water

Questions or Comments?

Call 1-866-344-5645or visit website at honestpharma.com